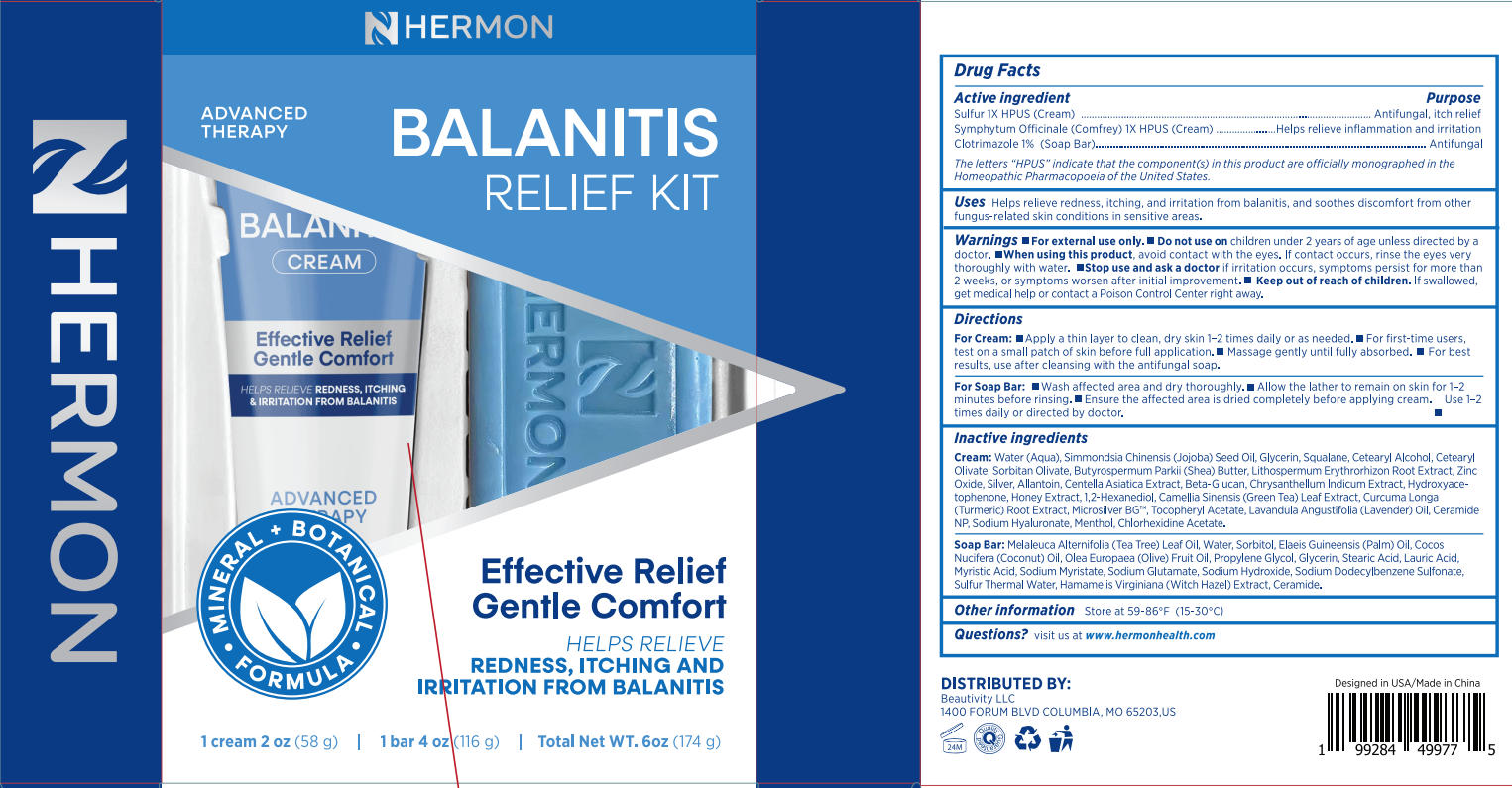 DRUG LABEL: Hermon Balanitis Cream
NDC: 85398-013 | Form: CREAM
Manufacturer: Beautivity LLC
Category: otc | Type: HUMAN OTC DRUG LABEL
Date: 20250901

ACTIVE INGREDIENTS: SULFUR 1 [hp_X]/58 g; SYMPHYTUM OFFICINALE WHOLE 1 [hp_X]/58 g
INACTIVE INGREDIENTS: BUTYROSPERMUM PARKII (SHEA) BUTTER; ALLANTOIN; LAVANDULA ANGUSTIFOLIA (LAVENDER) OIL; WATER; SORBITAN OLIVATE; ZINC OXIDE; SILVER PARTICLE (10 MICRON); SQUALANE; 1,2-HEXANEDIOL; .ALPHA.-TOCOPHEROL ACETATE; MENTHOL; SIMMONDSIA CHINENSIS (JOJOBA) SEED OIL; GLYCERIN; TRANSFORMING GROWTH FACTOR BETA RECEPTOR TYPE 3; CHRYSANTHELLUM INDICUM TOP; CETEARYL ALCOHOL; CETEARYL OLIVATE; LITHOSPERMUM ERYTHRORHIZON ROOT; SILVER; HYDROXYACETOPHENONE; CAMELLIA SINENSIS LEAF; CURCUMA LONGA (TURMERIC) ROOT; SODIUM HYALURONATE; CHLORHEXIDINE ACETATE; CENTELLA ASIATICA TRITERPENOIDS; HONEY; CERAMIDE NP

Initial Drug Listing - Hermon Balanitis Cream

ACTIVE INGREDIENT

- Sulfur 1X HPUS
- Symphytum Officinale (Comfrey) 1X HPUS

PURPOSE

- Antifungal. itch relief
- Helps relieve inflammation and irritation

DOSAGE AND ADMINISTRATION

Helps relieve redness, itching, and irritation from balanitis, and soothes discomfort from other
fungus-related skin conditions in sensitive areas.

WARNINGS

For external use only

DO NOT USE

children under 2 years of age unless directed by a doctor

WHEN USING

avoid contact with the eves. lf contact occurs, rinse the eyes very thoroughly with water

ASK DOCTOR

if irritation occurs, symptoms persist for more than 2 weeks, or symptoms worsen after initial improvement.

KEEP OUT OF REACH OF CHILDREN

lf swallowed,get medical help or contact a Poison Control Center right away.

INDICATIONS AND USAGE

- Apply a thin layer to clean, dry skin 1-2 times daily or as needed.
- For first-time users,test on a small patch of skin before full application.
- Massage gently until fully absorbed.
- For bestresults,use after cleansing with the antifungal soap.

INACTIVE INGREDIENT

Water (Aqua), Simmondsia Chinensis (jojoba) Seed Oil, Glycerin, Squalane, Cetearyl Alcohol, Cetearyl Olivate, Sorbitan Olivate, Butyrospermum Parkii (Shea) Butter, Lithospermum Erythrorhizon Root Extract, Zinc Oxide, Silver, Allantoin, Centella Asiatica Extract, Beta-Glucan, Chrysanthelum Indicum Extract, Hydroxyace-tophenone, Honey Extract, 1,2-Hexanediol, Camelia Sinensis (Green Tea) Leaf Extract, Curcuma Longa(Turmeric) Root Extract, Microsilver BG, Tocopheryl Acetate, Lavandula Angustifolia (Lavender) Oil, Ceramide NP, Sodium Hyaluronate, Menthol, Chlorhexidine Acetate.

OTHER SAFETY INFORMATION

Store at 59-86°F(15-30°C)

QUESTIONS

visit us at www.hermonhealth.com